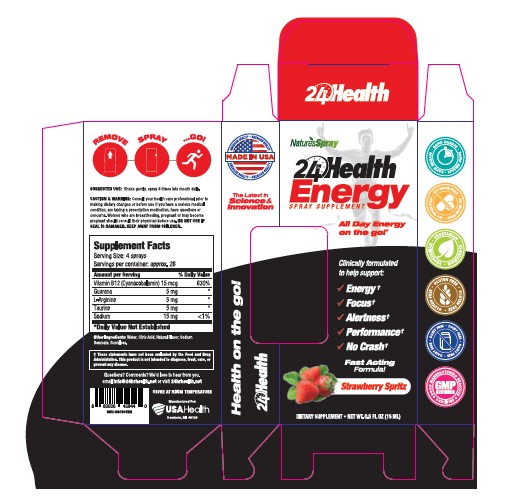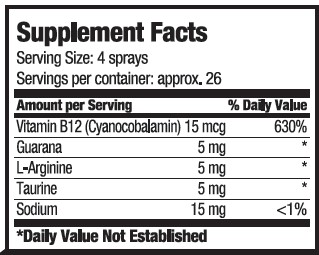 DRUG LABEL: 24hr Health Energy
NDC: 80893-004 | Form: SPRAY
Manufacturer: USA Health
Category: other | Type: Dietary Supplement
Date: 20201030

ACTIVE INGREDIENTS: sodium 15 mg/15 mL; TAURINE 5 mg/15 mL; ARGININE 5 mg/15 mL; GUARANA 5 mg/15 mL; CYANOCOBALAMIN 15 ug/15 mL
INACTIVE INGREDIENTS: water; CITRIC ACID MONOHYDRATE; SODIUM BENZOATE; SUCRALOSE

24hr Health Energy

Purpose

Clinically Formulated to help support

- Energy
- Focus
- Alertness
- Performance

No crash

Warning

Consult your healthcare professional prior to making dietary changes or before use if you have a serious medical condition, are taking a prescription medication, or have questions or concerns.

Precaution

Women who are breastfeeding, pregnant or may become pregnant should consult their physician before use.

Safe Handling

Do not use if seal is damaged. Keep out of reach of children.